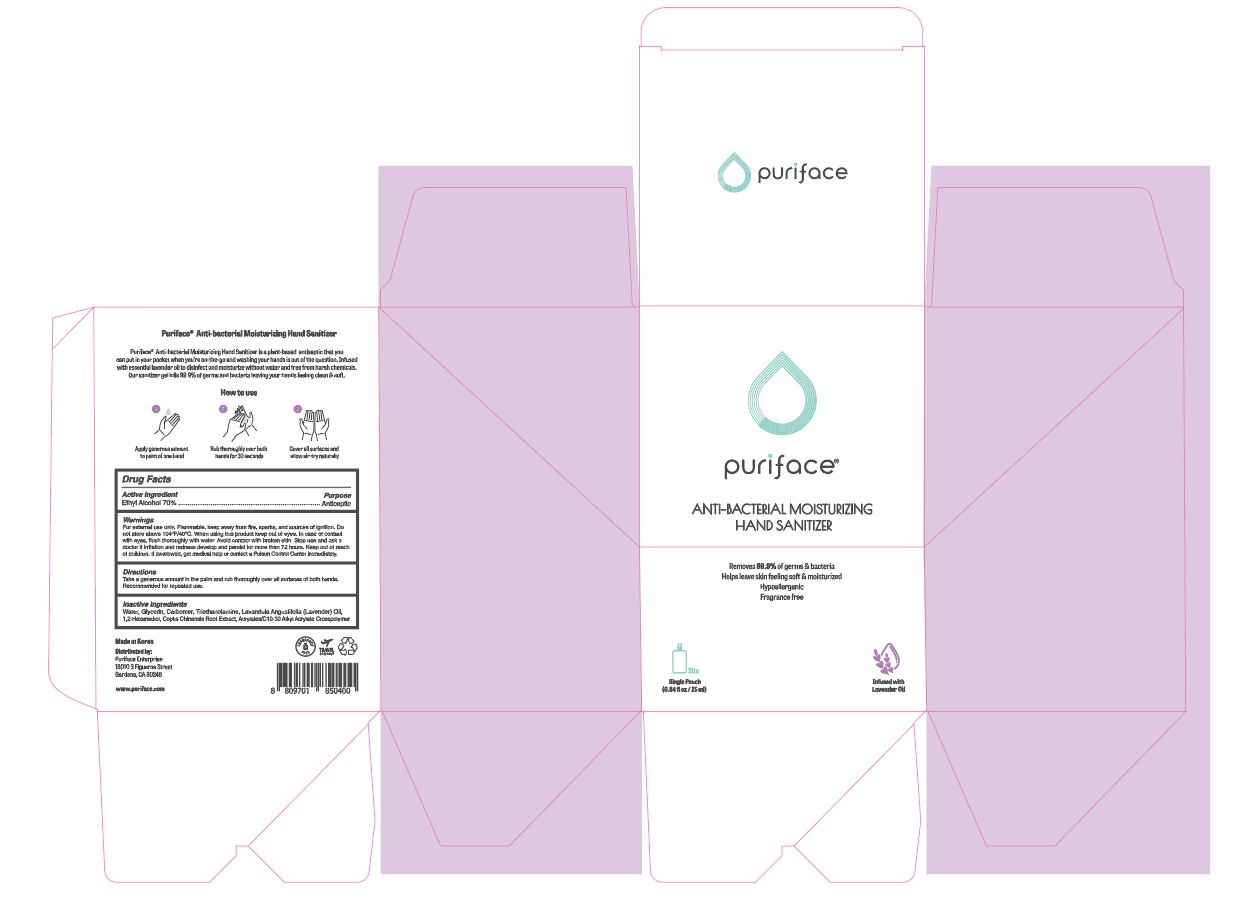 DRUG LABEL: PURIFACE ANTI-BACTERIAL MOISTURIZING HAND SANITIZER
NDC: 74004-025 | Form: GEL
Manufacturer: Ester Co., Ltd.
Category: otc | Type: HUMAN OTC DRUG LABEL
Date: 20200708

ACTIVE INGREDIENTS: ALCOHOL 17.5 mL/25 mL
INACTIVE INGREDIENTS: LAVENDER OIL; COPTIS CHINENSIS ROOT; CARBOMER INTERPOLYMER TYPE A (55000 CPS); 1,2-HEXANEDIOL; CARBOMER HOMOPOLYMER, UNSPECIFIED TYPE; WATER; TROLAMINE; GLYCERIN

[Ester Co., Ltd.-PURIFACE ANTI-BACTERIAL MOISTURIZING HAND SANITIZER]
25 mL pouch x 20 EA in box